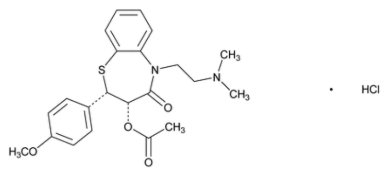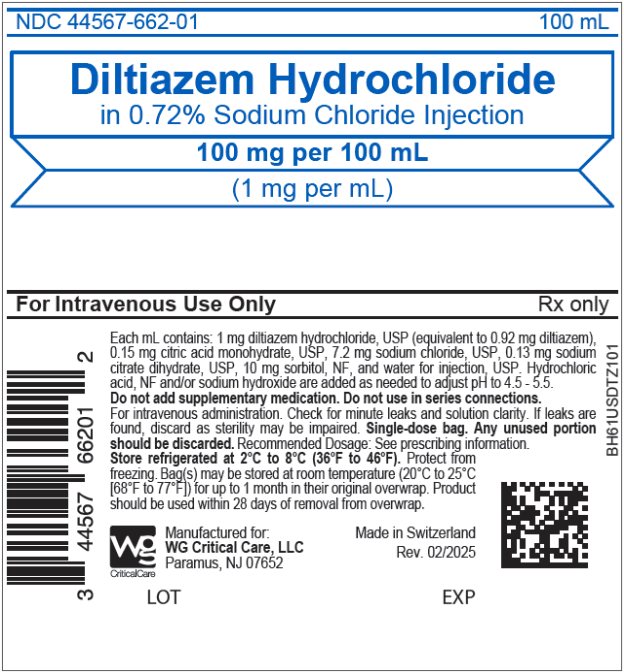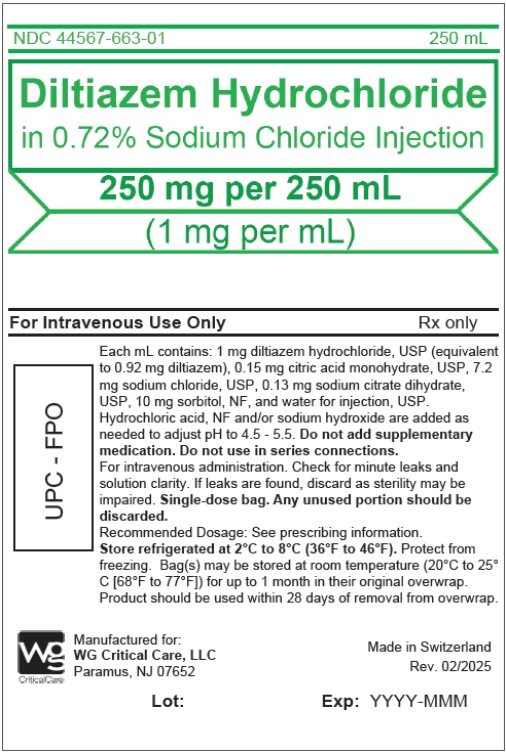 DRUG LABEL: DILTIAZEM HYDROCHLORIDE in SODIUM CHLORIDE
NDC: 44567-662 | Form: INJECTION, SOLUTION
Manufacturer: WG Critical Care, LLC
Category: prescription | Type: HUMAN PRESCRIPTION DRUG LABEL
Date: 20250415

ACTIVE INGREDIENTS: DILTIAZEM HYDROCHLORIDE 1 mg/1 mL
INACTIVE INGREDIENTS: CITRIC ACID MONOHYDRATE; WATER; SODIUM HYDROXIDE; HYDROCHLORIC ACID; SODIUM CHLORIDE; TRISODIUM CITRATE DIHYDRATE; SORBITOL

HIGHLIGHTS OF PRESCRIBING INFORMATION

These highlights do not include all the information needed to use DILTIAZEM HYDROCHLORIDE IN SODIUM CHLORIDE INJECTION safely and effectively. See full prescribing information for DILTIAZEM HYDROCHLORIDE IN SODIUM CHLORIDE INJECTION.
DILTIAZEM HYDROCHLORIDE IN SODIUM CHLORIDE injection, for intravenous use only
Initial U.S. Approval: 1982

1 INDICATIONS AND USAGE

Diltiazem Hydrochloride in Sodium Chloride Injection is a non-dihydropyridine calcium-channel blocker indicated for the following:

- Temporary control of rapid ventricular rate in atrial fibrillation or atrial flutter. (1.1)
- Rapid conversion of paroxysmal supraventricular tachycardias (PSVT) to sinus rhythm. (1.2)

2 DOSAGE AND ADMINISTRATION

Monitor ECG and blood pressure. The initial dose is 0.25 mg/kg or 20 mg intravenously over 2 minutes. If response is inadequate at 15 minutes, give one or more doses of 0.35 mg/kg or 25 mg intravenously over 2 minutes. Immediately following first bolus administration, begin intravenous infusion at 5 mg/hour. Increase by 5 mg/hour up to 15 mg/hour as needed and tolerated. (2.1, 2.2, 2.3)

Do not mix with other drugs. (2.4)

3 DOSAGE FORMS AND STRENGTHS

Injection: Clear, colorless solution in single-dose bag for intravenous use.

100 mg per 100 mL (1 mg/mL) and 250 mg per 250 mL (1 mg/mL) (3)

4 CONTRAINDICATIONS

- Sick sinus syndrome or second- or third-degree AV block with no functioning ventricular pacemaker. (4)
- Severe hypotension or cardiogenic shock. (4)
- Demonstrated hypersensitivity to the drug. (4)
- Atrial fibrillation or atrial flutter associated with an accessory bypass tract such as in Wolff-Parkinson-White (WPW). (4)
- Ventricular tachycardia. (4)

5 WARNINGS AND PRECAUTIONS

- Hemodynamic deterioration and ventricular fibrillation if administered to patients with wide complex tachycardia of ventricular origin. (5.2)
- Second-or third-degree AV block. (5.3)
- Heart failure. (5.4)
- Hypotension. (5.5)

6 ADVERSE REACTIONS

Most common adverse reactions are hypotension, itching and burning at injection site, vasodilation, and arrhythmia. (6)

To report SUSPECTED ADVERSE REACTIONS, contact WG Critical Care, LLC at 1-866-562-4708, or FDA at 1-800-FDA-1088 or www.fda.gov/medwatch.

7 DRUG INTERACTIONS

- Anesthetics: Further depression of cardiac contractility, conductivity, and automaticity as well as vascular dilation. (7)
- Beta-Blockers: Monitor for bradycardia, AV block, and depression of contractility. (7)
- Clonidine: Increased risk of bradycardia. (7)
- CYP3A4 Inducers: Avoid concomitant use. (7)
- CYP3A4 Inhibitors: Monitor diltiazem’s pharmacologic effect. (7)
- CYP3A4: substrates: Increased exposure of substrates. (7)
- Ivabradine: Avoid concomitant use. (7)
- Ranolazine: Limit ranolazine to 500 mg twice daily. (7)
- Statins: Avoid statins metabolized by CYP3A4. (7)

FULL PRESCRIBING INFORMATION

1 INDICATIONS AND USAGE

1.1 Atrial Fibrillation or Atrial Flutter

Diltiazem Hydrochloride in Sodium Chloride Injection is indicated in adults for the temporary control of rapid ventricular rate in atrial fibrillation or atrial flutter.

1.2 Paroxysmal Supraventricular Tachycardia

Diltiazem Hydrochloride in Sodium Chloride Injection is indicated in adults for rapid conversion of paroxysmal supraventricular tachycardias (PSVT) to sinus rhythm.

2 DOSAGE AND ADMINISTRATION

2.1 General Considerations

Administer intravenous diltiazem in a setting with continuous monitoring of the ECG and frequent measurement of blood pressure. A defibrillator and emergency equipment should be readily available.

Diltiazem Hydrochloride in Sodium Chloride Injection is a ready to administer product that requires no further dilution prior to infusion. Parenteral drug products should be inspected visually for particulate matter and discoloration prior to administration whenever solution and container permit.

2.2 Intravenous Single Injection

The initial dose of diltiazem hydrochloride should be 0.25 mg/kg actual body weight administered over 2 minutes (20 mg is a reasonable dose for the average patient). If response is inadequate, a second dose may be administered after 15 minutes. The second dose of diltiazem hydrochloride should be 0.35 mg/kg actual body weight administered over 2 minutes (25 mg is a reasonable dose for the average patient). Subsequent intravenous bolus doses should be individualized.

2.3 Continuous Intravenous Infusion

Immediately following bolus, the recommended initial infusion rate of diltiazem hydrochloride is 5 mg/hour. Adjust the infusion rate in 5 mg/hour increments up to a maximum of 15 mg/hour as needed to achieve satisfactory rate control. Infusions longer than 24 hours have not been studied. Patients should generally be transitioned to other antiarrhythmic agents within 24 hours [see Clinical Studies (14)].

2.4 Physical Incompatibilities

Do not mix diltiazem hydrochloride with any other drugs in the same container. If possible, use a dedicated line for diltiazem hydrochloride.

Diltiazem hydrochloride has demonstrated physical incompatibilities with acetazolamide, acyclovir, aminophylline, ampicillin, ampicillin sodium/sulbactam sodium, cefamandole, cefoperazone, diazepam, furosemide, hydrocortisone sodium succinate, insulin (regular: 100 units/mL), methylprednisolone sodium succinate, mezlocillin, nafcillin, phenytoin, rifampin, and sodium bicarbonate.

3 DOSAGE FORMS AND STRENGTHS

Injection: Clear, colorless solution in a single-dose bag for intravenous use.

100 mg per 100 mL (1 mg/mL)

250 mg per 250 mL (1 mg/mL)

4 CONTRAINDICATIONS

Diltiazem Hydrochloride in Sodium Chloride Injection is contraindicated in the following situations:

- Patients with sick sinus syndrome or second- or third-degree AV block except in the presence of a functioning ventricular pacemaker.
- Patients with severe hypotension or cardiogenic shock.
- Patients who have demonstrated hypersensitivity to the drug.
- Concomitant administration with IV beta-blockers.
- Patients with atrial fibrillation or atrial flutter associated with an accessory bypass tract such as in WPW syndrome.
- Patients with ventricular tachycardia.

5 WARNINGS AND PRECAUTIONS

5.1 Tachycardia and Hypotension in patients with AF/AFL and accessory bypass tract

Diltiazem may cause ventricular fibrillation if given to patients in atrial fibrillation or atrial flutter associated with an accessory bypass tract such as in WPW syndrome. Distinguish atrial fibrillation with aberrancy (bundle branch block) from pre-excited atrial fibrillation prior to diltiazem administration [see Contraindications (4)].

5.2 Hemodynamic Deterioration in Patients with Wide Complex Tachycardia

Diltiazem may cause hemodynamic deterioration and ventricular fibrillation if administered to patients with wide complex tachycardia of ventricular origin. Distinguish wide complex QRS tachycardia of supraventricular origin from that of ventricular origin prior to diltiazem administration [see Contraindications (4)].

5.3 AV Block

Diltiazem prolongs AV nodal conduction and refractoriness that may cause second- or third-degree AV block in sinus rhythm. Concomitant use of diltiazem with agents known to affect cardiac conduction may result in additive effects [see Drug Interactions (7)]. If high-degree AV block occurs in sinus rhythm, discontinue diltiazem and institute appropriate supportive measures [see Overdosage (10)].

5.4 Heart Failure

Diltiazem is a negative inotrope and can cause decreased systolic function and heart failure. Do not initiate in patients with acute decompensated heart failure or cardiogenic shock. If heart failure develops during diltiazem treatment, discontinue treatment and treat heart failure appropriately.

5.5 Hypotension

Diltiazem can cause symptomatic hypotension. Patients with low blood pressure at baseline and those on concomitant medications that decrease blood pressure, intravascular volume, or myocardial contractility are at increased risk for hypotension.

6 ADVERSE REACTIONS

The following adverse reaction rates are based on the use of diltiazem hydrochloride injection in over 400 domestic clinical trial patients with atrial fibrillation/flutter or PSVT under double-blind or open-label conditions.

Hypotension was the most commonly reported adverse event during clinical trials, with symptomatic hypotension occurring in 3.2% of patients. Other events reported in a least 1% of the diltiazem-treated patients were injection site reactions (e.g., itching, burning) - 3.9%, vasodilation (flushing) - 1.7%, and arrhythmia (junctional rhythm or isorhythmic dissociation) - 1%.

In addition, the following events were reported infrequently (less than 1%):

Gastrointestinal - Constipation, elevated SGOT or alkaline phosphatase, nausea, vomiting

Nervous System - Dizziness

Other - dyspnea, edema, headache,

Although not observed in clinical trials with diltiazem hydrochloride injection, the following events associated with oral diltiazem may occur:

Dermatologic - Erythema multiforme (including Stevens-Johnson syndrome, toxic epidermal necrolysis), exfoliative dermatitis, petechiae, photosensitivity, purpura, pruritus, rash, urticaria, acute generalized exanthematous pustulosis,

Gastrointestinal - Anorexia, dysgeusia, dyspepsia

Other - Allergic reactions, angioedema (including facial or periorbital edema), gingival hyperplasia, hyperglycemia, impotence.

7 DRUG INTERACTIONS

Table 1. Clinically Relevant Interactions with Diltiazem

Drug/Substance Class or Name | Clinical implication | Prevention/Management
Agents Known to decrease peripheral resistance, cardiac contractility or conduction | Increased risk of bradycardia, AV block, and heart failure. | Monitor.
Beta-blockers | Increased risk of bradycardia, AV block, and depression of contractility. | Beta-blocker may need to be decreased [see Warnings and Precautions (5.1, 5.2)].
Anesthetics | Depressed cardiac contractility, conductivity, and automaticity as well as the vascular dilation. | Monitor.
Clonidine | Increased risk of bradycardia. | Monitor.
Drugs metabolized by Cytochrome P450 3A4 | Diltiazem is both a substrate and an inhibitor of the cytochrome P450 3A4 enzyme system. Concomitant use with diltiazem can increase exposure of drugs that are substrates of CYP450 3A4. | Drugs that are substrates of CYP450 3A4 may require dose adjustment to maintain optimum therapeutic blood levels.
Benzodiazepines | Increased exposure likely. | Monitor.
Buspirone | Increased exposure likely. | Monitor.
Carbamazepine | Increased exposure likely. | Monitor.
Cyclosporine | Increased exposure likely. | Monitor.
Quinidine | Increased exposure likely. | Monitor.
Ranolazine | Increased exposure likely. | Limit ranolazine to 500 mg twice daily.
Statins | Increased risk of myopathy and rhabdomyolysis with statins metabolized by CYP3A4. | When possible, use a non-CYP3A4-metabolized statin with diltiazem.; Limit daily dose of simvastatin to 10 mg and diltiazem to 240 mg [see Clinical Pharmacology (12.3)].
Ivabradine | May exacerbate bradycardia and conduction disturbances. | Avoid concomitant use [see Clinical Pharmacology (12.3)].
Effect of other drugs on Diltiazem
Cytochrome P450 3A4 Inhibitors/ Inducers | Diltiazem is a substrate of the cytochrome P450 3A4 enzyme and inhibitors/inducers may change the pharmacological effect of diltiazem | Monitor.
Strong or moderate CYP 3A inhibitors a; Examples b: Ketoconazole, itraconazole, cimetidine | Patients currently receiving diltiazem therapy should be carefully monitored for a change in pharmacological effect when initiating and discontinuing therapy with strong or moderate inhibitors of CYP3A4. | An adjustment in the diltiazem dose may be warranted
CYP inducers; Examples b: Rifampin, carbamazepine | CYP3A inducers can lower the plasma levels of diltiazem. | Coadministration of diltiazem with rifampin or any known CYP3A4 inducer should be avoided when possible, and alternative therapy considered [see Clinical Pharmacology (12.3)].

a Strong and moderate inhibitors increase the AUC of sensitive substrates of CYP3A4 by ≥ 5 and ≥ 2-fold, respectively
b These examples are a guide and not considered a comprehensive list of all possible drugs that may fit this category. The healthcare provider should consult appropriate references for comprehensive information.

8 USE IN SPECIFIC POPULATIONS

8.1 Pregnancy

Risk Summary

The available data from the published literature over decades of use with diltiazem during pregnancy have not identified a drug associated risk of major birth defects, miscarriage, or adverse maternal or fetal outcomes. In animal reproduction studies, decreased embryo and fetal survival rates, and skeletal abnormalities have been observed at oral doses five to ten times the human oral antianginal therapeutic dose, and reduction in pup weights was also observed. At 20 times the human oral antianginal therapeutic dose, an increase in stillbirths was observed (see Data).

The estimated background risk for major birth defects and miscarriage for the indicated population is unknown. All pregnancies have a background risk of birth defect, loss, or other adverse outcomes. In the U.S. general population, the estimated background risks of major birth defects and miscarriage in clinically recognized pregnancies are 2% to 4% and 15% to 20%, respectively.

Data

Animal Data

Reproduction studies have been conducted in mice, rats, and rabbits. Administration of oral doses ranging from five to ten times greater (on a mg/kg basis) than the human oral antianginal therapeutic dose has resulted in embryo and fetal lethality. These doses, in some studies, have been reported to cause skeletal abnormalities. In the perinatal/postnatal studies there was some reduction in early individual pup weights and survival rates. There was an increased incidence of stillbirths at doses of 20 times the human oral antianginal therapeutic dose or greater.

8.2 Lactation

Risk Summary

Published literature reports the presence of diltiazem in human milk. One report with oral diltiazem suggests that concentrations in breast milk may approximate serum levels. There are no data on the effects of diltiazem on the breastfed child or the effects on milk production. The developmental and health benefits of breastfeeding should be considered along with the mother’s clinical need for Diltiazem Hydrochloride Injection and any potential adverse effects on the breastfed child from Diltiazem Hydrochloride Injection or from the underlying maternal condition.

8.4 Pediatric Use

Safety and effectiveness in pediatric patients have not been established.

8.5 Geriatric Use

Clinical studies of diltiazem did not include sufficient numbers of subjects aged 65 and over to determine whether they respond differently from younger subjects. Other reported clinical experience has not identified differences in responses between the elderly and younger patients. In general, dose selection for an elderly patient should be cautious, usually starting at the low end of the dosing range, reflecting the greater frequency of decreased hepatic, renal, or cardiac function, and of concomitant disease or other drug therapy.

10 OVERDOSAGE

Overdosage experience is limited. In the event of overdosage or an exaggerated response, appropriate supportive measures should be employed.

Diltiazem does not appear to be removed by peritoneal or hemodialysis. Limited data suggest that plasmapheresis may hasten diltiazem elimination following overdose.

The intravenous LD50's in mice and rats were 60 and 38 mg/kg, respectively. The toxic dose in humans is not known.

11 DESCRIPTION

Diltiazem Hydrochloride in Sodium Chloride Injection is a non-dihydropyridine calcium channel-blocker. Diltiazem hydrochloride is 1,5-benzothiazepin-4(5H)one,3-(acetyloxy)-5-[2-(dimethylamino)ethyl]-2, 3-dihydro-2-(4-methoxyphenyl)-, monohydrochloride, (+)-cis- with the molecular weight of 450.98 and structural formula:

Molecular formula: C22H26N204S.HCl

Diltiazem hydrochloride is a white to off-white crystalline powder with a bitter taste soluble in water, methanol, and chloroform.

Diltiazem Hydrochloride in Sodium Chloride Injection is a clear, colorless, sterile, nonpyrogenic, isotonic solution for intravenous use only. It is packaged in single-dose bags containing 100 mg/100 mL and 250 mg/250 mL. Each mL contains: 1 mg diltiazem hydrochloride, USP (equivalent to 0.92 mg diltiazem), 0.15 mg citric acid monohydrate, USP, 7.2 mg sodium chloride, USP, 0.13 mg sodium citrate dihydrate, USP, 10 mg sorbitol, NF, and water for injection, USP. Hydrochloric acid, NF and/or sodium hydroxide are added as needed to adjust pH to 4.5 - 5.5.

12 CLINICAL PHARMACOLOGY

12.1 Mechanism of Action

The therapeutic effects of diltiazem are believed to be related to inhibiting influx of calcium ions during membrane depolarization of cardiac and vascular smooth muscle.

Paroxysmal Supraventricular Tachycardia: Diltiazem slows AV nodal conduction time and prolongs AV nodal refractoriness. Diltiazem exhibits frequency- (use-) dependent effects on AV nodal conduction such that it may selectively reduce the heart rate during tachycardias involving the AV node with little or no effect on normal AV nodal conduction at normal heart rates.

Atrial Fibrillation or Atrial Flutter: Diltiazem slows the ventricular rate in patients with a rapid ventricular response during atrial fibrillation or atrial flutter. Diltiazem converts paroxysmal supraventricular tachycardia (PSVT) to normal sinus rhythm by interrupting the reentry circuit in AV nodal reentrant tachycardias and reciprocating tachycardias.

Diltiazem prolongs the sinus cycle length. It has no effect on the sinus node recovery time or on the sinoatrial conduction time in patients without SA nodal dysfunction. Diltiazem has no significant electrophysiologic effect on tissues in the heart that are fast sodium channel dependent, e.g., His-Purkinje tissue, atrial and ventricular muscle, and extra nodal accessory pathways.

Like other calcium channel antagonists, because of its effect on vascular smooth muscle, diltiazem decreases total peripheral resistance resulting in a decrease in both systolic and diastolic blood pressure.

12.2 Pharmacodynamics

Intravenous diltiazem hydrochloride 20 mg prolongs AH conduction time and AV node functional and effective refractory periods by approximately 20%. PR in healthy volunteers and HR in patients with atrial fibrillation and atrial flutter are dependent on plasma level of diltiazem. Based on this relationship, the mean plasma diltiazem concentration required to produce a 20%, 30% and 40% decrease in heart rate was determined to be 80 ng/mL, 130 ng/mL and 300 ng/mL, respectively.

In patients with cardiovascular disease, diltiazem hydrochloride administered intravenously in single bolus doses, followed in some cases by a continuous infusion, reduced blood pressure, systemic vascular resistance, the rate-pressure product, and coronary vascular resistance and increased coronary blood flow. In a limited number of studies of patients with compromised myocardium (severe congestive heart failure, acute myocardial infarction, hypertrophic cardiomyopathy), administration of intravenous diltiazem produced no significant effect on contractility, left ventricular end diastolic pressure, or pulmonary capillary wedge pressure. The mean ejection fraction and cardiac output/index remained unchanged or increased. Maximal hemodynamic effects usually occurred within 2 to 5 minutes of an injection. However, in rare instances, worsening of congestive heart failure has been reported in patients with preexisting impaired ventricular function.

12.3 Pharmacokinetics

Based on the results of pharmacokinetic studies in healthy volunteers administered different oral diltiazem hydrochloride formulations, constant rate intravenous infusions of diltiazem hydrochloride at 3, 5, 7, and 11 mg/h are predicted to produce steady-state plasma diltiazem concentrations equivalent to 120-, 180-, 240-, and 360-mg total daily oral doses of diltiazem hydrochloride tablets and diltiazem hydrochloride extended-release capsules.

Distribution

The volume of distribution of diltiazem is approximately 305 L. Diltiazem is 70% to 80% bound to plasma proteins. In vitro studies suggest alpha1-acid glycoprotein binds approximately 40% of the drug at clinically significant concentrations. Albumin appears to bind approximately 30% of the drug, while other constituents bind the remaining bound fraction. Competitive in vitro ligand binding studies have shown that diltiazem hydrochloride binding is not altered by therapeutic concentrations of digoxin, phenytoin, hydrochlorothiazide, indomethacin, phenylbutazone, propranolol, salicylic acid, tolbutamide, or warfarin.

Metabolism and Excretion

Diltiazem is extensively metabolized in the liver. After oral administration, diltiazem undergoes extensive metabolism in man by deacetylation, N-demethylation, and O-demethylation via cytochrome P-450 (oxidative metabolism) in addition to conjugation. Metabolites N-monodesmethyldiltiazem, desacetyldiltiazem, desacetyl-N-monodesmethyldiltiazem, desacetyl-O-desmethyldiltiazem, and desacetyl-N, O-desmethyldiltiazem have been identified in human urine. These metabolites are also observed following 24-hour constant rate intravenous infusion.

The systemic clearance of diltiazem has been found to be decreased in patients with atrial fibrillation or atrial flutter, compared to healthy volunteers. In patients administered continuous infusions at 10 mg/h or 15 mg/h for 24 h, diltiazem systemic clearance averaged 42 L/h and 31 L/h, respectively. The plasma elimination half-life is approximately 3.4 h. Total radioactivity measurement following short IV administration in healthy volunteers suggests the presence of other unidentified metabolites which attain higher concentrations than those of diltiazem and are more slowly eliminated; half-life of total radioactivity is about 20 h compared to 2 to 5 h for diltiazem.

After constant rate intravenous infusion to healthy male volunteers, diltiazem exhibits nonlinear pharmacokinetics over an infusion range of 4.8 to 13.2 mg/h for 24 h. Over this infusion range, as the dose is increased, systemic clearance decreases from 64 to 48 L/h while the plasma elimination half-life increases from 4.1 to 4.9 h. The volume of distribution remains unchanged (360 to 391 L).

Specific Populations

Renal insufficiency, or even end-stage renal disease, does not appear to influence diltiazem disposition following oral administration. Liver cirrhosis reduces diltiazem's apparent clearance and prolong its half-life.

Drug Interaction Studies

Effect of Diltiazem on Other Drugs:

Agents known to Decrease Peripheral Resistance, Cardiac Contractility and Conduction

Beta-blockers: Controlled and uncontrolled domestic studies suggest that concomitant use of diltiazem and beta-blockers is usually well tolerated, but available data are not sufficient to predict the effects of concomitant treatment in patients with left ventricular dysfunction or cardiac conduction abnormalities. Administration of diltiazem concomitantly with propranolol in five normal volunteers resulted in increased propranolol levels in all subjects and bioavailability of propranolol was increased approximately 50%. In vitro, propranolol appears to be displaced from its binding sites by diltiazem [see Warnings and Precautions (5.2, 5.3)].

Digitalis: Intravenous diltiazem has been administered to patients receiving either intravenous or oral digitalis therapy. The combination of the two drugs was well tolerated without serious adverse effects.

Ivabradine: Coadministration with diltiazem resulted in approximately 3-fold the AUC and Cmax of ivabradine and 20-60% increase in the active metabolite (S18982) exposure [see Drug Interactions (7)].

CYP3A4 Substrates

Benzodiazepines: With diltiazem, the AUC of midazolam and triazolam is 3- to 4-fold and the Cmax is 2-fold what they are alone. The elimination half-life of midazolam and triazolam also increased by 50-150% during coadministration with diltiazem [see Drug Interactions (7)].

Buspirone: With diltiazem, the mean buspirone AUC was about 5.5-fold and Cmax was about 4.1-fold what they are alone. The t1/2 and Tmax of buspirone were not affected by diltiazem [see Drug Interactions (7)].

Carbamazepine: Concomitant administration of diltiazem with carbamazepine was reported to result in elevated serum levels of carbamazepine (40% to 72% increase), resulting in toxicity in some cases [see Drug Interactions (7)].

Cyclosporine: In renal and cardiac transplant recipients, a reduction of cyclosporine dose ranging from 15% to 48% was necessary to maintain cyclosporine trough concentrations similar to those seen prior to the addition of diltiazem. If these agents are to be administered concurrently, cyclosporine concentrations should be monitored, especially when diltiazem therapy is initiated, adjusted, or discontinued. The effect of cyclosporine on diltiazem plasma concentrations has not been evaluated [see Drug Interactions (7)].

Quinidine: Diltiazem increases the AUC of quinidine by 51%, elimination half-life by 36%, and decreases its oral clearance by 33% [see Drug Interactions (7)].

Ranolazine: On coadministration with diltiazem 180 to 360 mg daily, the plasma levels of ranolazine are 2.2-to 2.8-fold what they are alone. Diltiazem plasma levels are not affected by ranolazine [see Drug Interactions (7)].

Statins: Diltiazem has been shown to increase the AUC of some statins. The risk of myopathy and rhabdomyolysis with statins metabolized by CYP3A4 may be increased with concomitant use of diltiazem [see Drug Interactions (7)].

Coadministration of a simvastatin with 120 mg BID diltiazem SR resulted in 5 times the mean simvastatin AUC versus simvastatin alone. Higher doses of diltiazem are likely to be worse.

Coadministration of a lovastatin with 120 mg BID diltiazem SR resulted in a 3 to 4 times the mean lovastatin AUC and Cmax versus lovastatin alone. In the same study, there was no significant change in AUC and Cmax of 20 mg single dose pravastatin during diltiazem coadministration. Diltiazem plasma levels were not significantly affected by lovastatin or pravastatin.

Effect of Other Drugs on Diltiazem:

CYP3A4 Inhibitors and Inducers

Cimetidine and Ranitidine: Coadministration with cimetidine increased Cmax of diltiazem by 58% and AUC by 53%. Ranitidine produced smaller, non-significant increases. The effect may be mediated by cimetidine's known inhibition of hepatic CYP3A, the enzyme system responsible for the first-pass metabolism of diltiazem [see Drug Interactions (7)].

Rifampin: Coadministration of rifampin with diltiazem lowered the diltiazem plasma concentrations to undetectable levels [see Drug Interactions (7)].

13 NONCLINICAL TOXICOLOGY

13.1 Carcinogenesis, Mutagenesis, Impairment of Fertility

A 24-month study in rats at oral dosage levels of up to 100 mg/kg/day and a 21-month study in mice at oral dosage levels of up to 30 mg/kg/day showed no evidence of carcinogenicity. There was also no mutagenic response in vitro or in vivo in mammalian cell assays or in vitro in bacteria. No evidence of impaired fertility was observed in a study performed in male and female rats at oral dosages of up to 100 mg/kg/day.

14 CLINICAL STUDIES

In domestic controlled trials in patients with atrial fibrillation or atrial flutter, bolus administration of diltiazem hydrochloride injection was effective in reducing heart rate by at least 20% in 95% of patients. Diltiazem hydrochloride injection rarely converts atrial fibrillation or atrial flutter to normal sinus rhythm. Following administration of one or two intravenous bolus doses of diltiazem injection, response usually occurs within 3 minutes and maximal heart rate reduction generally occurs in 2 to 7 minutes. Heart rate reduction may last from 1 to 3 hours. If hypotension occurs, it is generally short-lived, but may last from 1 to 3 hours.

A 24-hour continuous infusion of diltiazem injection in the treatment of atrial fibrillation or atrial flutter maintained at least a 20% heart rate reduction during the infusion in 83% of patients. Upon discontinuation of infusion, heart rate reduction may last from 0.5 hours to more than 10 hours (median duration 7 hours). Hypotension, if it occurs, may be similarly persistent.

In the controlled clinical trials, 3.2% of patients required some form of intervention (typically, use of intravenous fluids or the Trendelenburg position) for blood pressure support following diltiazem hydrochloride injection.

In domestic controlled trials, bolus administration of diltiazem hydrochloride injection was effective in converting PSVT to normal sinus rhythm in 88% of patients within 3 minutes of the first or second bolus dose.

Symptoms associated with the arrhythmia were improved in conjunction with decreased heart rate or conversion to normal sinus rhythm following administration of diltiazem hydrochloride injection.

In controlled clinical trials, therapy with antiarrhythmic agents to maintain reduced heart rate in atrial fibrillation or atrial flutter or for prophylaxis of PSVT was generally started within 3 hours after bolus administration of diltiazem hydrochloride. These antiarrhythmic agents were intravenous or oral digoxin, Class 1 antiarrhythmics (e.g., quinidine, procainamide), calcium channel blockers, and oral beta-blockers.

16 HOW SUPPLIED/STORAGE AND HANDLING

Diltiazem Hydrochloride in Sodium Chloride Injection is supplied as a clear, colorless solution in a single-dose bag with an aluminum overwrap available as:

Total Strength per Total Volume | Strength per mL | Carton of 10 single-dose bags NDC | Bag and Overwrap NDC
100 mg per 100 mL | 1 mg/mL | 44567-662-10 | 44567-662-01
250 mg per 250 mL | 1 mg/mL | 44567-663-10 | 44567-663-01

Discard any unused portion.

Store under refrigeration at 2°C to 8°C (36°F to 46°F). Do not freeze. The single-dose bags in their original overwraps may be stored for up to one month at 20°C to 25°C [68°F to 77°F], [See USP Controlled Room Temperature]. The bag and port are not made with natural rubber latex, PVC, or DEHP.

Product should be used within 28 days of removal from aluminum overwrap.

Manufactured for:
WG Critical Care, LLC
Paramus, NJ 07652

Made in Switzerland

PACKAGE/LABEL PRINCIPAL DISPLAY PANEL

NDC 44567-662-01
Diltiazem Hydrochloride
in 0.72% Sodium Chloride Injection
100 mg per 100 mL
(1 mg per mL)

PACKAGE/LABEL PRINCIPAL DISPLAY PANEL

NDC 44567-663-01
Diltiazem Hydrochloride
in 0.72% Sodium Chloride Injection
250 mg per 250 mL
(1 mg per mL)